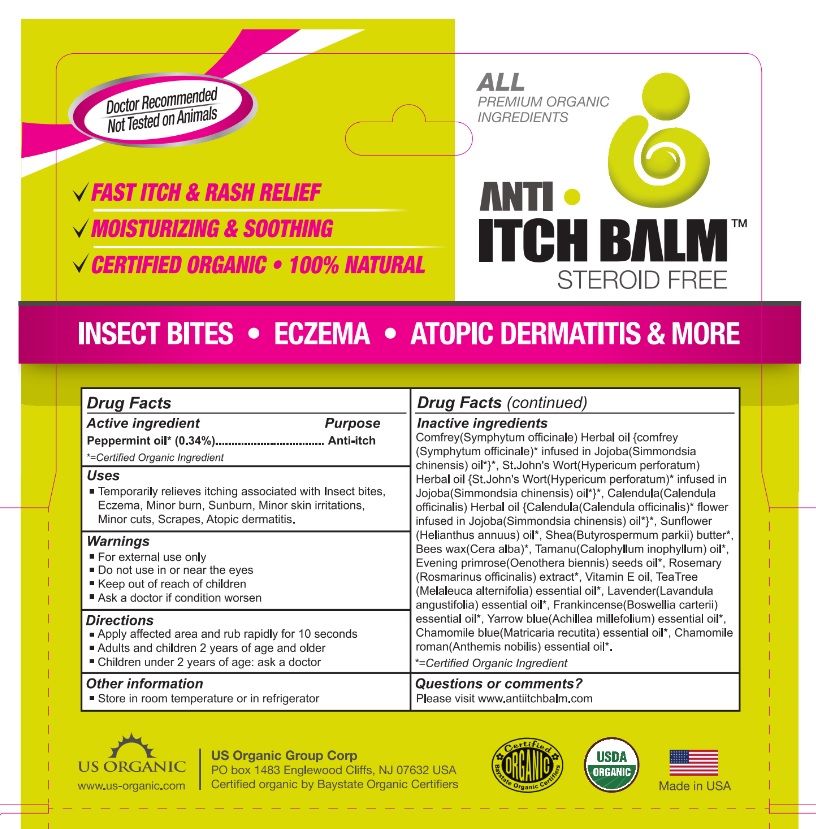 DRUG LABEL: Anti Itch Balm
                
NDC: 57285-100 | Form: OINTMENT
Manufacturer: US ORGANIC GROUP CORP
Category: otc | Type: HUMAN OTC DRUG LABEL
Date: 20130329

ACTIVE INGREDIENTS: Peppermint Oil 0.0952 g/28 g
INACTIVE INGREDIENTS: JOJOBA OIL; SUNFLOWER OIL; SHEA BUTTER; YELLOW WAX; TAMANU OIL; EVENING PRIMROSE OIL; ROSEMARY OIL; .ALPHA.-TOCOPHEROL; LAVENDER OIL; TEA TREE OIL; CHAMOMILE FLOWER OIL; CHAMAEMELUM NOBILE FLOWER OIL; FRANKINCENSE OIL; ACHILLEA MILLEFOLIUM

Drug Facts

ACTIVE INGREDIENT

Peppermint Oil* ---------- 0.34%

*=Certified Organic Ingredient

PURPOSE

Anti-Itch

INDICATIONS AND USAGE

Temporarily relieves itching associated with Insect bites, Eczema, Minor burn, Sunburn, Minor skin irritations, minor cuts, scrapes, atopic dermatitis.

Ask a doctor if condition worsen

Keep out of reach of children.

WARNINGS

- For external use only

- Do not use in or near the eyes

- Keep out of reach of children

- Ask a doctor if condition worsen

INSTRUCTIONS FOR USE

- Apply affected area and rub rapidly for 10 seconds

- Adults and children 2 years of age and older

- Children under 2 years of age: ask a doctor

DOSAGE AND ADMINISTRATION

Apply affected area and rub rapidly for 10 seconds.

INACTIVE INGREDIENT

Simmondsiachinensis (Organic Jojoba oil)*,Helianthus annuus (Organic Sunflower oil)*,Butyrospermumparkii (Organic Shea butter)*,Cera alba (Organic Bees wax)*,Calophylluminophyllum (Organic Tamanu oil)*,Oenotherabiennis (Organic Evening primerose oil)*,Rosemarinusoficinalis (Organic Rosemary) extract*,Vitamin E Oil,Lavandulaangustifolia (Organic Lavender essential oil)*,Melaleucaalternifolia (Organic Tea tree essential oil)*,Matricariarecutita (Organic Chamomile blue essential oil)*,Anthemisnobilis (Organic Chamomile roman essential oil)*,Boswelliacarterii (Organic Frankincense essential oil)*,Achilleamillefolium (Organic Yarrow blue essential oil)*
*= Certified Organic Ingredient